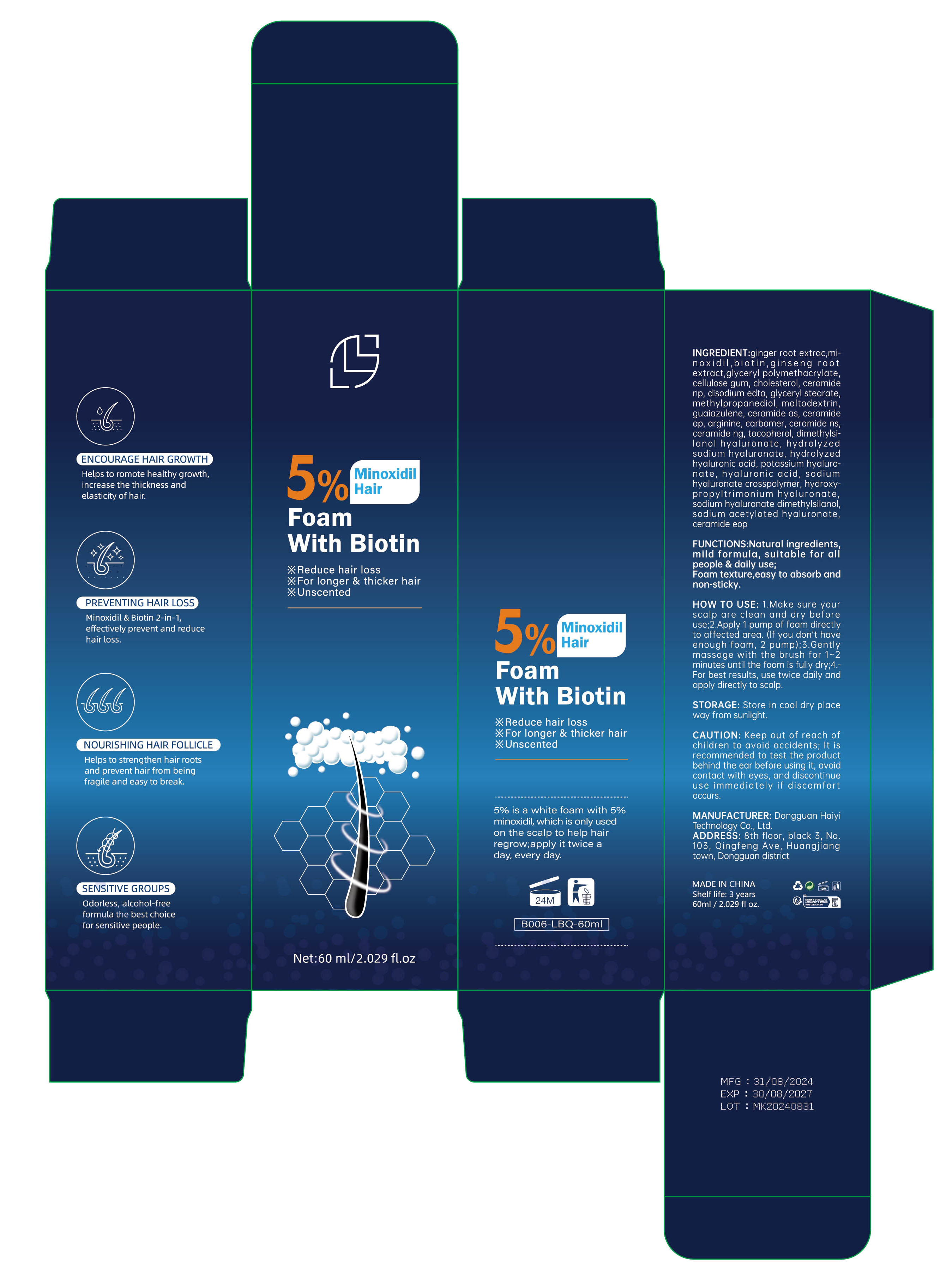 DRUG LABEL: 5 MINOXIDIL HAIR FOAM WITH BIOTIN
NDC: 84732-045 | Form: SPRAY
Manufacturer: Dongguan Haiyi Technology Co.,Ltd.
Category: otc | Type: HUMAN OTC DRUG LABEL
Date: 20241014

ACTIVE INGREDIENTS: GINGER 1 mg/100 mL
INACTIVE INGREDIENTS: MINOXIDIL; CERAMIDE NP; CARBOXYMETHYLCELLULOSE SODIUM, UNSPECIFIED FORM; GUAIAZULENE; DISODIUM EDTA-COPPER; GLYCERYL POLYMETHACRYLATE (300000 MPA.S); ASIAN GINSENG; MALTODEXTRIN; BIOTIN; GLYCERYL STEARATE SE; METHYLPROPANEDIOL; CHOLESTEROL

Active ingredient

ginger root extrac

Inactive ingredient

mi-noxidil,biotin,ginseng rootextract,glyceryl polymethacrylate,cellulose gum, cholesterol, ceramidenp, disodium edta, glyceryl stearate.methylpropanediol,maltodextrin,guaiazulene, ceramide as, ceramideap, arginine, carbomer, ceramide nsceramide ng, tocopherol, dimethylsi-lanol hyaluronate,hydrolyzedsodium hyaluronate, hydrolyzedhyaluronic acid, potassium hyaluro.nate,hyaluronic acid,sodiumhyaluronate crosspolymer, hydroxy-propyltrimonium hyaluronate.sodium hyaluronate dimethylsilanolsodium acetylated hyaluronate.ceramide eop

Purpose section

Natural ingredientsmild formula, suitable for allpeople & daily use;

Foam texture,easy to absorb andnon-sticky

Warning

Keep out of reach ofchildren to avoid accidents; lt isrecommended to test the productbehind the ear before using it, avoidcontact with eyes, and discontinueuse immediately if discomfortoccurs.

stop use

This product may cause allergic reactions in asmall number of people.
lf youexperience any discomfort,please stop using it immediately.

not use

Not suitable for use by children, pregnantor breast feeding people.

OUT OF CHILDREN

KEEP THE PRODUCT OUT OF REACH OF CHILDREN to

HOW TO USE

1.Make sure yourscalp are clean and dry beforeuse;

2.Apply 1 pump of foam directlyto affected area. (lf you don't haveenough foam,2 pump);

3.Gentlymassage with the brush for 1~2minutes until the foam is fully dry;4.For best results, use twice daily andapply directly to scalp.

Dosage

apply it twice aday, every day.